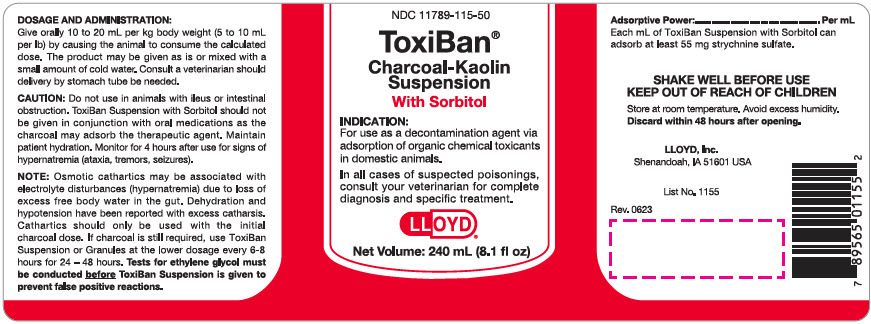 DRUG LABEL: ToxiBan With Sorbitol
NDC: 11789-115 | Form: SUSPENSION
Manufacturer: LLOYD, Inc. of Iowa
Category: animal | Type: OTC ANIMAL DRUG LABEL
Date: 20230711

ACTIVE INGREDIENTS: ACTIVATED CHARCOAL 55 [arb'U]/1 mL
INACTIVE INGREDIENTS: SORBITOL; KAOLIN; METHYLPARABEN

ToxiBan® With Sorbitol

VETERINARY INDICATIONS

INDICATION:

For use as a decontamination agent via adsorption of organic chemical toxicants in domestic animals.

In all cases of suspected poisonings, consult your veterinarian for complete diagnosis and specific treatment.

DOSAGE AND ADMINISTRATION:

Give orally 10 to 20 ml per kg body weight (5 to 10 ml per lb) by causing the animal to consume the calculated dose. The product may be given as is or mixed with a small amount of cold water. Consult a veterinarian should delivery by stomach tube be needed.

PRECAUTIONS

CAUTION: Do not use in animals with ileus or intestinal obstruction. ToxiBan Suspension with Sorbitol should not be given in conjunction with oral medications as the charcoal may adsorb the therapeutic agent. Maintain patient hydration. Monitor for 4 hours after use for signs of hypernatremia (ataxia, tremors, seizures).

NOTE: Osmotic cathartics may be associated with electrolyte disturbances (hypernatremia) due to loss of excess free body water in the gut. Dehydration and hypotension have been reported with excess catharsis. Cathartics should only be used with the initial charcoal dose. If charcoal is still required, use ToxiBan Suspension or Granules at the lower dosage every 6-8 hours for 24 - 48 hours. Tests for ethylene glycol must be conducted before ToxiBan Suspension is given to prevent false positive reactions.

Adsorptive Power:........................ Per ml

Each ml of ToxiBan Suspension with Sorbitol can adsorb at least 55 mg strychnine sulfate.

STORAGE AND HANDLING

SHAKE WELL BEFORE USE

KEEP OUT OF REACH OF CHILDREN

Store at room temperature. Avoid excess humidity.

Discard within 48 hours after opening.

LLOYD, lnc.
Shenandoah, IA 51601 USA

List No. 1155

Rev. 0623

PRINCIPAL DISPLAY PANEL - 240 mL Bottle Label

NDC 11789-115-50

ToxiBan®

Charcoal-Kaolin
Suspension
With Sorbitol

INDICATION:

For use as a decontamination agent via
adsorption of organic chemical toxicants
in domestic animals.

In all cases of suspected poisonings,
consult your veterinarian for complete
diagnosis and specific treatment.

LLOYD®

Net Volume: 240 mL (8.1 fl oz)